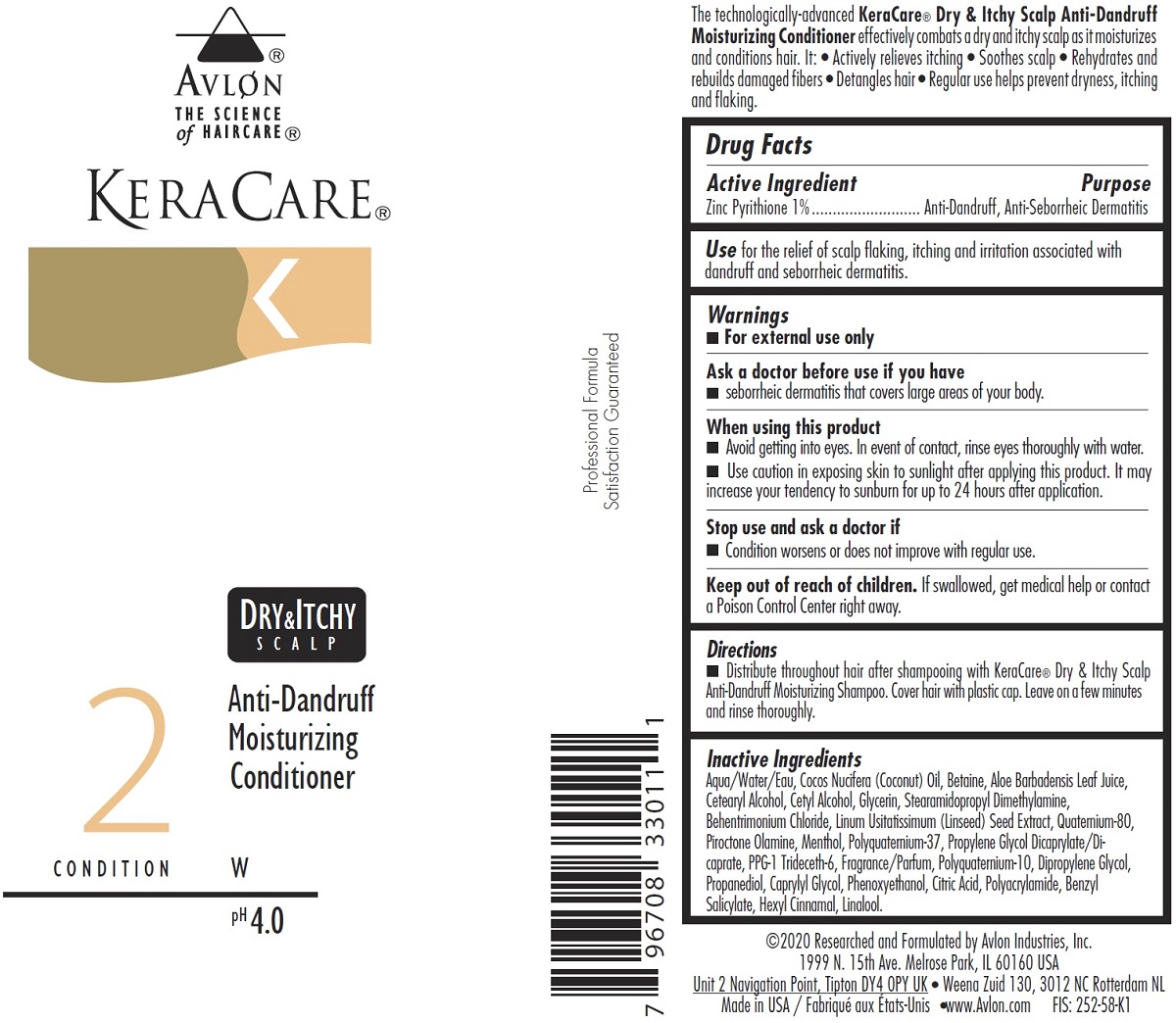 DRUG LABEL: KeraCare Dry and Itchy Scalp Anti-Dandruff
NDC: 63766-003 | Form: LOTION
Manufacturer: Avlon Industries, Inc.
Category: otc | Type: HUMAN OTC DRUG LABEL
Date: 20241009

ACTIVE INGREDIENTS: PYRITHIONE ZINC 10 mg/1 mL
INACTIVE INGREDIENTS: COCONUT OIL; BETAINE; ALOE VERA LEAF; CETOSTEARYL ALCOHOL; PIROCTONE OLAMINE; PPG-1 TRIDECETH-6; PROPANEDIOL; CAPRYLYL GLYCOL; BENZYL SALICYLATE; .ALPHA.-HEXYLCINNAMALDEHYDE; PHENOXYETHANOL; LINALOOL, (+/-)-; GLYCERIN; STEARAMIDOPROPYL DIMETHYLAMINE; MENTHOL; PROPYLENE GLYCOL DICAPRYLATE/DICAPRATE; DIPROPYLENE GLYCOL; CITRIC ACID MONOHYDRATE; WATER; FLAX SEED; 2-(CYCLOHEXYLAMINO)ETHANESULFONIC ACID; CETYL ALCOHOL; BEHENTRIMONIUM CHLORIDE

KeraCare Dry and Itchy Scalp Anti-Dandruff Moisturizing Conditioner

Active Ingredient

Pyrithione Zinc 1%

Purpose

Anti-Dandruff, Anti-Seborrheic Dermatitis

INDICATIONS AND USAGE

Use for the relief of scalp flaking, itching and irritation associated with

dandruff and seborrheic dermatitis.

Warnings

■ For external use only

-----------------------------------------------------------------------------------------------------

Ask a doctor before use if you have

■ seborrheic dermatitis that covers large areas of your body.

-----------------------------------------------------------------------------------------------------

When using this product

■ Avoid getting into eyes. In event of contact, rinse eyes thoroughly with water.

■ Use caution in exposing skin to sunlight after applying this product. It may

increase your tendency to sunburn for up to 24 hours after application.

-----------------------------------------------------------------------------------------------------

Stop use and ask a doctor if

■ Condition worsens or does not improve with regular use.

-----------------------------------------------------------------------------------------------------

Keep out of reach of children. If swallowed, get medical help or contact

a Poison Control Center right away.

Directions

For best results, shampoo first with KeraCare® Dry & Itchy Scalp Anti-Dandruff Moisturizing
Shampoo. Distribute KeraCare® Dry & Itchy Scalp Anti-Dandruff Moisturizing Conditioner
throughout hair and cover with a plastic cap. Leave on a few minutes and rinse thoroughly. Style
as usual.

Inactive Ingredients

Aqua/Water/Eau, Cocos Nucifera (Coconut) Oil, Betaine, Aloe Barbadensis Leaf Juice, Cetearyl
Alcohol, Cetyl Alcohol, Glycerin, Stearamidopropyl Dimethylamine, Behentrimonium Chloride,
Linum Usitatissimum (Linseed) Seed Extract, Quaternium-80, Piroctone Olamine, Menthol,
Polyquaternium-37, Propylene Glycol Dicaprylate/Dicaprate, PPG-1 Trideceth-6,
Fragrance/Parfum, Polyquaternium-10, Dipropylene Glycol, Propanediol, Caprylyl Glycol,
Phenoxyethanol, Citric Acid, Polyacrylamide, Benzyl Salicylate, Hexyl Cinnamal, Linalool.

PACKAGE LABEL

KeraCare Dry and Itchy Scalp Anti-Dandruff Moisturizing Conditioner

Product NDC 63766-003